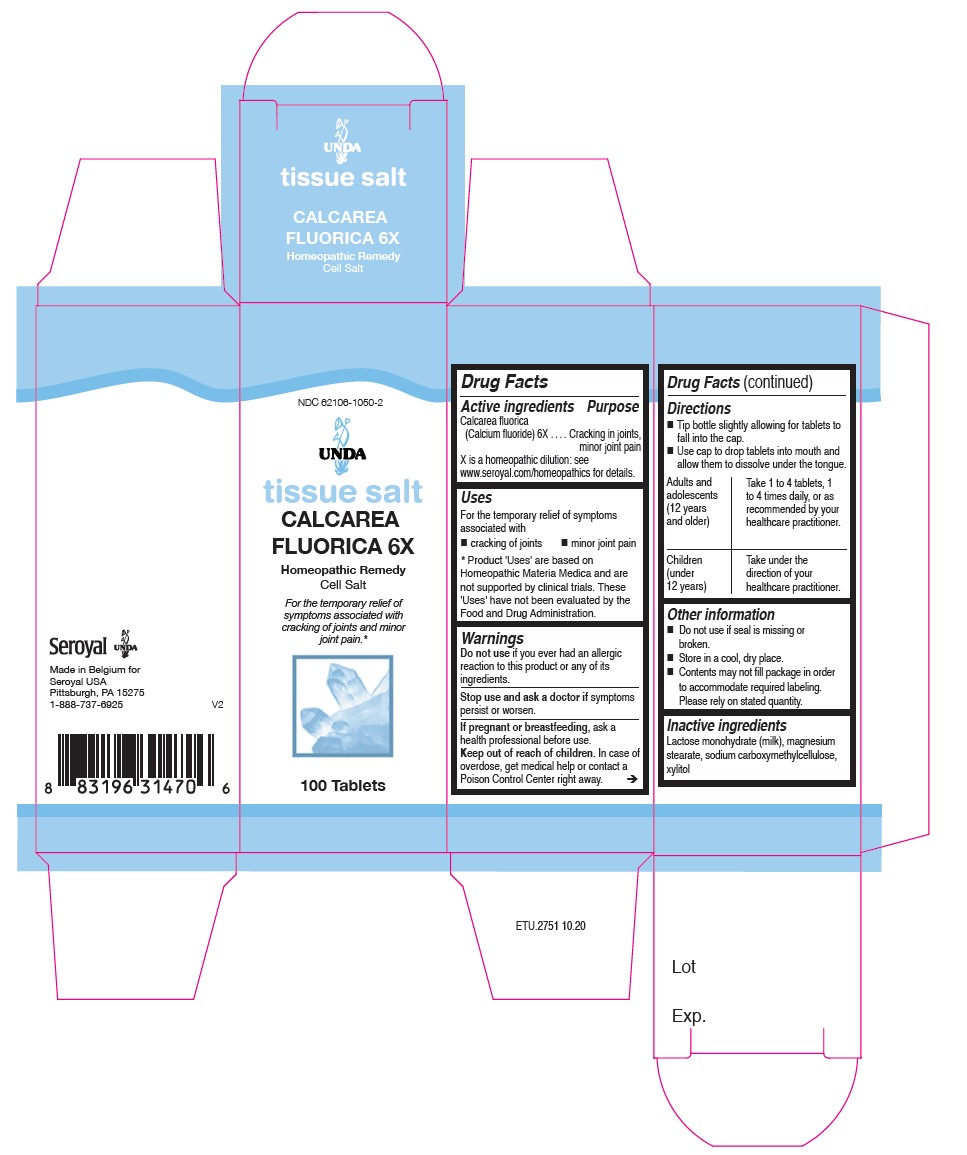 DRUG LABEL: CALCAREA FLUORICA 6X
NDC: 62106-1050 | Form: TABLET
Manufacturer: Seroyal USA
Category: homeopathic | Type: HUMAN OTC DRUG LABEL
Date: 20210714

ACTIVE INGREDIENTS: CALCIUM FLUORIDE 6 [hp_X]/1 1
INACTIVE INGREDIENTS: CARBOXYMETHYLCELLULOSE SODIUM; MAGNESIUM STEARATE; LACTOSE MONOHYDRATE; XYLITOL

CALCAREA FLUORICA 6X

Active Ingredients

Calcarea fluorica (Calcium fluoride) 6X

Uses

For the temporary relief of symptoms associated

with cracking of joints and minor joint pain.

Warnings

Do not use if you ever had an allergic reaction to this product or any of its ingredients.

Stop use and ask a doctor if symptoms persist or worsen.

If pregnant or breastfeeding, ask a healthcare practitioner before use.
Keep out of reach of children.

In case of overdose, get medical help or contact
a Poison Control Center right away.

PREGNANCY OR BREAST FEEDING

If pregnant or breastfeeding, ask a healthcare practitioner before use.

Keep out of reach of children.

OVERDOSAGE

In case of overdose, get medical help or contact

a Poison Control Center right away.

Stop use and ask a doctor if symptoms persist or worsen.

Inactive Ingredients:

Lactose monohydrate (milk),

magnesium stearate,

sodium carboxymethylcellulose,

xylitol

Directions

Tip bottle slightly allowing for tablets to fall into the cap.

Use cap to drop tablets into mouth and allow them to dissolve under the tongue.

Adults and adolescents (12 years and older)

Take 1 to 4 tablets, one to four times daily, or as recommended by your healthcare practitioner.

Children (under 12 years)

Take under the direction of your healthcare practitioner.

Uses

For the temporary relief of symptoms associated

with cracking of joints and minor joint pain.

Directions

Tip bottle slightly allowing for tablets to fall into the cap.
Use cap to drop tablets into mouth and allow them to dissolve under the tongue.
Adults and Adolescents (12 years and older): Take 1 to 4 tablets, one to
four times daily, or as recommended by your healthcare practitioner.

Children (under 12 years): Take under the direction of your healthcare practitioner.

Other information
Do not use if seal is missing or broken.
Store in a cool, dry place.

Contents may not fill package in order
to accommodate required labeling.
Please rely on stated quantity.

PACKAGE LABEL

NDC 62016-1050-2

UNDA

tissue salt

CALCAREA FLUORICA 6X

Homeopathic Preparation

Cell Salt

For the temporary relief of symptoms associated

with cracking of joints and minor joint pain.

100 Tablets